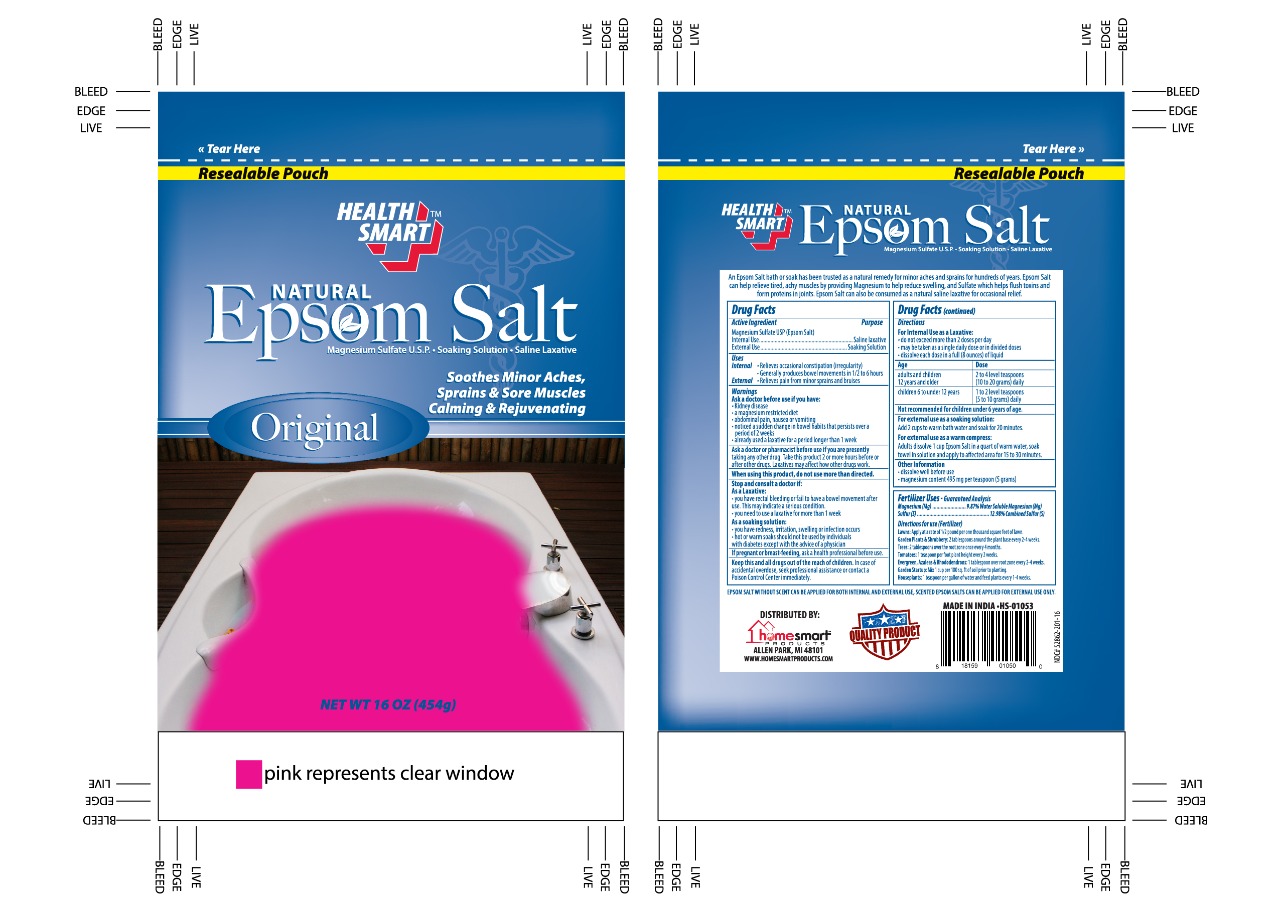 DRUG LABEL: Epsom Salts
NDC: 52862-202 | Form: GRANULE
Manufacturer: International Wholesale Inc.
Category: otc | Type: HUMAN OTC DRUG LABEL
Date: 20241219

ACTIVE INGREDIENTS: MAGNESIUM SULFATE HEPTAHYDRATE 100 g/100 g

Health Smart Epsom Salts

Active Ingredients Purpose

Magnesium Sulfate (heptahydrate) 100% Saline Laxative

Uses

- For relief of Occasional Constipation (Irregularity)
- This product generally produces bowel movement

Keep out of reach of children. In case of overdose, get medical help or contact a Poison Control Center right away.

Ask a doctor or pharmacist before use if you are taking any other drug. Take this product 2 or more hours before or after any other drugs. Laxative may affect how other drugs work.

Warnings

Ask a doctor before use if you have

- Kidney Disease
- A magnesium restricted diet
- Abdominal pain, nausea or vomiting
- Noticed a sudden change in bowel habits that persists over a period of 2 weeks
- Already used a laxative for a period of longer than 1 week

If pregnant or breast-feeding ask a health profesional before use

Directions

- do not exceed more than 2 doses per day
- drink a full glass (8 ounces) of liquid with each dose
- dissolve the dose in 8 ounces of water. Lemon juice may be added to improve the taste.
- adults and children 12 years and over: 2 to 4 level teaspoons (10 to 20 grams) daily
- children 6 to under 12 years: 1 to 2 level teaspoons (5 to 10 grams) daily
- children under 6 years: consult a doctor

There are no inactive ingredients

PACKAGE LABEL

Health Smart

Mutli purpose

Epsom Salts

Net Wt. 16 oz (454 g)